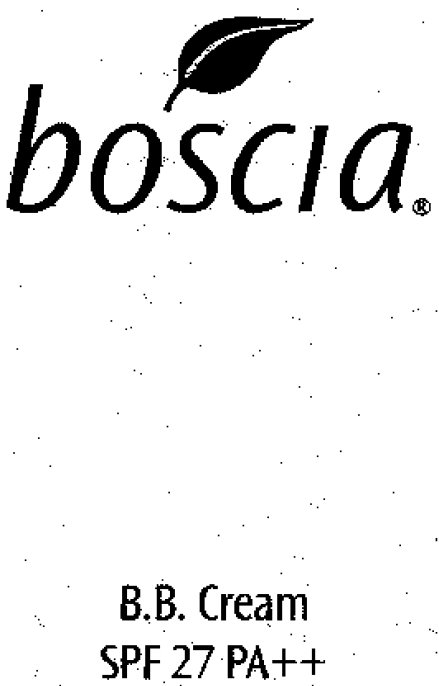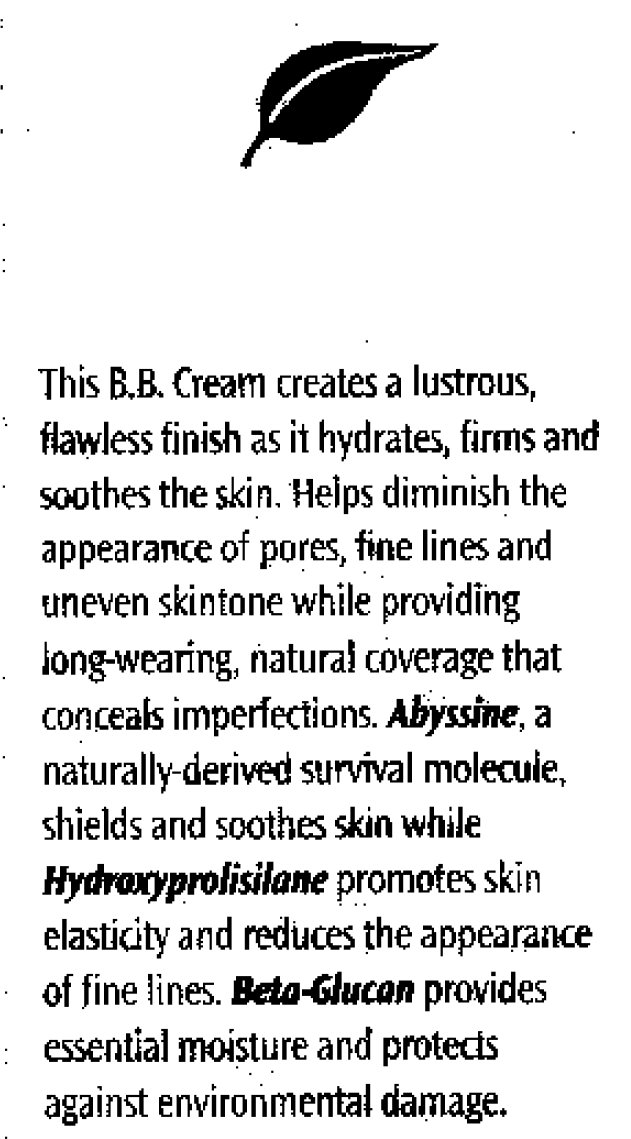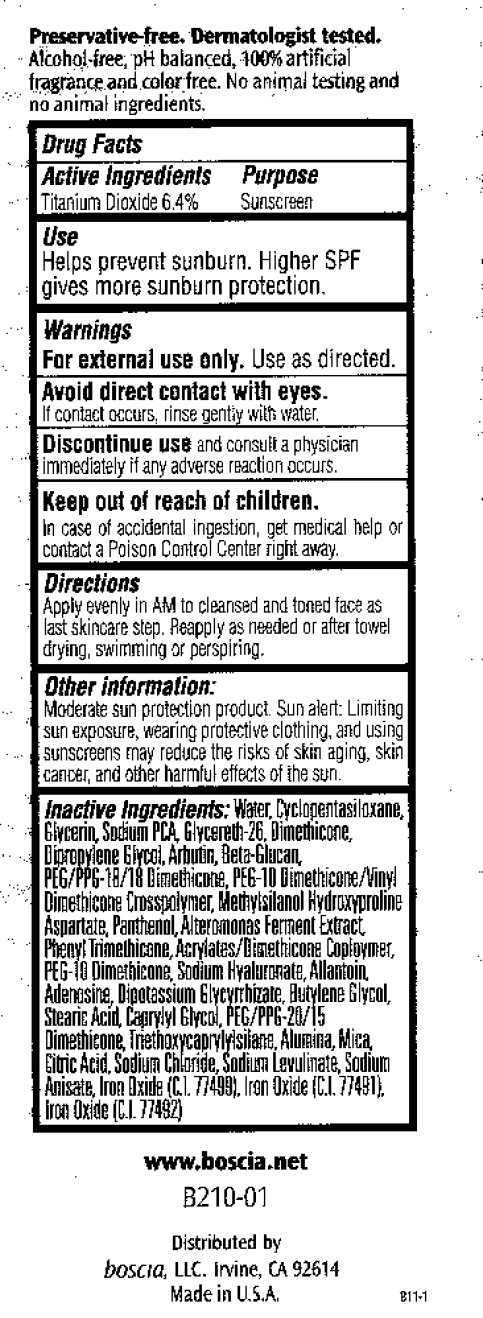 DRUG LABEL: Boscia BB SPF 27 PA
NDC: 76151-210 | Form: CREAM
Manufacturer: Boscia LLC
Category: otc | Type: HUMAN OTC DRUG LABEL
Date: 20231212

ACTIVE INGREDIENTS: TITANIUM DIOXIDE 6.4 g/100 g
INACTIVE INGREDIENTS: WATER; CYCLOMETHICONE 5; GLYCERIN; SODIUM PYRROLIDONE CARBOXYLATE; GLYCERETH-26; DIMETHICONE; DIPROPYLENE GLYCOL; ARBUTIN; PANTHENOL; PHENYL TRIMETHICONE; HYALURONATE SODIUM; BUTYLENE GLYCOL; STEARIC ACID; CAPRYLYL GLYCOL; TRIETHOXYCAPRYLYLSILANE; ALUMINUM OXIDE; MICA; CITRIC ACID MONOHYDRATE; SODIUM CHLORIDE; SODIUM ANISATE; FERROSOFERRIC OXIDE; FERRIC OXIDE RED; FERRIC OXIDE YELLOW

Boscia BB Cream SPF 27 PA++

Active Ingredients Purpose Titanium Dioxide 6.4% Sunscreen

PURPOSE

Use Helps prevent sunburn. Higher SPF gives more sunburn protection.

Warnings For external use only. Use as directed.

WHEN USING

Avoid direct contact with eyes. If contact occurs, rinse gently with water.

STOP USE

Discontinue use and consult a physician immediately if any adverse reaction occurs.

KEEP OUT OF REACH OF CHILDREN

In case of accidental ingestion, get medical help or contact a Poison Control Center right away.

OTHER SAFETY INFORMATION

In case of accidental ingestion, get medical help or contact a Poison Control Center right away.

DOSAGE AND ADMINISTRATION

Directions Apply in AM to cleansed and toned face as last skincare step. Reapply as needed or after towel drying, swimming or perspiring.

Other Information: Moderate sun protection product. Sun alert: Limiting sun exposure, wearing protective clothing, and using sunscreens may reduce the risks of skin aging, skin cancer, and other harmful effects of the sun.

INACTIVE INGREDIENT

Inactive Ingredients: Water, Cyclopentasiloxane, Glycerin, Sodium PCA, Glycereth-26, Dimethicone, Dipropylene Glycol, Arbutin, Beta-Glucan, PEG/PPG-18/18 Dimethicone, PEG-10 Dimethicone/Vinyl Dimethicone Crosspolymer, Methylsilanol Hydroxyproline Aspartate, Panthenol, Alteromonas Ferment Extract, Phenyl Trimethicone, Acrylates/Dimethicone Copolymer, PEG-10 Dimethicone, Sodium Hyaluronate, Allantoin Adehosine, Dipotassium Glycyrihizate, Butylene Glycol, Stearic Acid, Caprylyl Glycol, PEG/PPG-20/15 Dimethicone, Triethoxycaprylylsilane, Alumina, Mica, Citric Acid, Sodium Chloride, Sodium Levulinate, Sodium Anisate, Iron Oxide (C.I. 77499), Iron Oxide (C.I. 77491), Iron Oxide (C.I. 77492)

DESCRIPTION

This B.B. Cream creates a lustrous, flawless finish as it hydrates, firms and soothes the skin. Helps diminish the appearance of pores, fine lines and uneven skintone while providing long-wearing, natural coveage that conceals imperfections. Abyssine, a naturally-derived survival molecule, shields and soothes skin while Hydroxyprolisilane promotes skin elasticity and reduces the appearance of fine lines. Beta-Glucon provides essential moisture and protects against environmental damage.

Preservative-free. Dermatologist tested. Alcohol-free, pH balanced, 100% artificial fragrance and color free. No animal testing and no animal ingredients. www.boscia.net B210-01 Distributed by boscia, LLC. Irvine, CA 92614 Made in U.S.A. B11-1

Use

Helps prevent sunburn. Higher SPF gives more sunburn protection.

PACKAGE LABEL

boscia B.B. Cream SPF 27 PA++

PACKAGE LABEL

This B.B. Cream creates a lustrous, flawless finish as it hydrates, firms and soothes the skin. Helps diminish the appearance of pores, fine lines and uneven skintone while providing long-wearing, natural coveage that conceals imperfections. Abyssine, a naturally-derived survival molecule, shields and soothes skin while Hydroxyprolisilane promotes skin elasticity and reduces the appearance of fine lines. Beta-Glucon provides essential moisture and protects against environmental damage.

PACKAGE LABEL

Preservative-free. Dermatologist tested. Alcohol-free, pH balanced, 100% artificial fragrance and color free. No animal testing and no animal ingredients. www.boscia.net B210-01 Distributed by boscia, LLC. Irvine, CA 92614 Made in U.S.A. B11-1